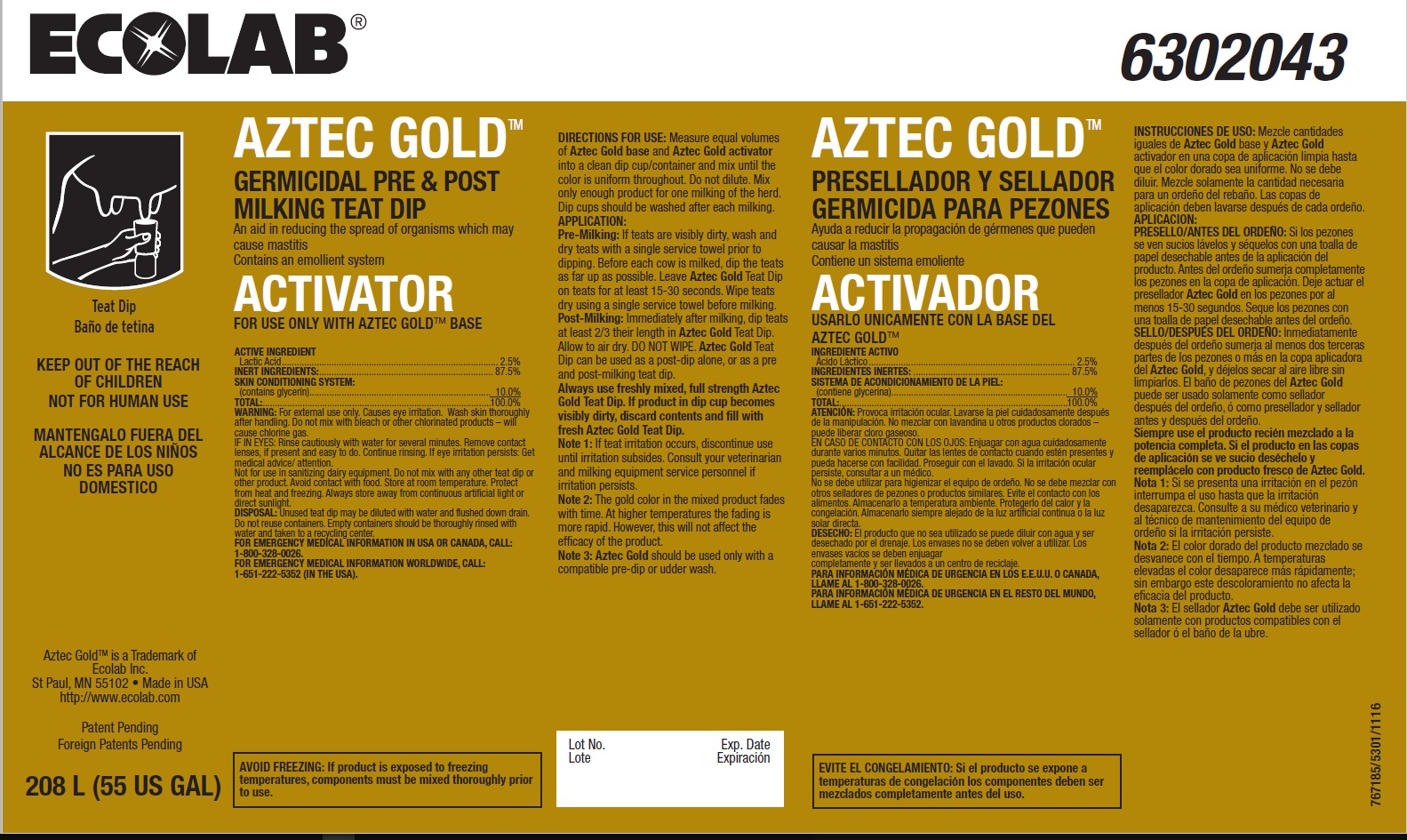 DRUG LABEL: Aztec Gold Activator
NDC: 47593-610 | Form: SOLUTION
Manufacturer: Ecolab Inc.
Category: animal | Type: OTC ANIMAL DRUG LABEL
Date: 20190709

ACTIVE INGREDIENTS: LACTIC ACID 25 mg/1 mL
INACTIVE INGREDIENTS: WATER; GLYCERIN

SAFE HANDLING WARNING

KEEP OUT OF THE REACH OF CHILDREN

NOT FOR HUMAN USE

AVOID FREEZING: If product is exposed to freezing temperatures, components must be mixed thoroughly prior to use.

WARNING: For external use only. Causes eye irritation. Wash skin thoroughly after handling. Do not mix with bleach or other chlorinated products – will cause chlorine gas.

DISPOSAL: Unused teat dip may be diluted with water and flushed down drain. Do not reuse containers. Empty containers should be thoroughly rinsed with water and taken to a recycling center.

VETERINARY INDICATIONS

DIRECTIONS FOR USE: Measure equal volumes of Aztec Gold base and Aztec Gold activator into a clean dip cup/container and mix until the color is uniform throughout. Do not dilute. Mix only enough product for one milking of the herd. Dip cups should be washed after each milking.

APPLICATION:

Pre-Milking: If teats are visibly dirty, wash and dry teats with a single service towel prior to dipping. Before each cow is milked, dip the teats as far up as possible. Leave Aztec Gold Teat Dip on teats for at least 15-30 seconds. Wipe teats dry using a single service towel before milking.

Post-Milking: Immediately after milking, dip teats at least 2/3 their length in Aztec Gold Teat Dip. Allow to air dry. DO NOT WIPE. Aztec Gold Teat Dip can be used as a post-dip alone, or as a pre and post-milking teat dip.

Always use freshly mixed, full strength Aztec Gold Teat Dip. If product in dip cup becomes visibly dirty, discard contents and fill with fresh Aztec Gold Teat Dip.

Note 1: If teat irritation occurs, discontinue use until irritation subsides. Consult your veterinarian and milking equipment service personnel if irritation persists.

Note 2: The gold color in the mixed product fades with time. At higher temperatures the fading is more rapid. However, this will not affect the efficacy of the product.

Note 3: Aztec Gold should be used only with a compatible pre-dip or udder wash.

OTHER SAFETY INFORMATION

IF IN EYES: Rinse cautiously with water for several minutes. Remove contact lenses, if present and easy to do. Continue rinsing. If eye irritation persists: Get medical advice/ attention.

Not for use in sanitizing dairy equipment. Do not mix with any other teat dip or other product. Avoid contact with food. Store at room temperature. Protect from heat and freezing. Always store away from continuous artificial light or direct sunlight.

FOR EMERGENCY MEDICAL INFORMATION IN USA OR CANADA, CALL: 1-800-328-0026.

FOR EMERGENCY MEDICAL INFORMATION WORLDWIDE, CALL: 1-651-222-5352 (IN THE USA).

PACKAGE LABEL

AZTEC GOLD

GERMICIDAL PRE & POST

MILKING TEAT DIP

An aid in reducing the spread of organisms which may cause mastitis

Contains an emollient system

ACTIVATOR

FOR USE ONLY WITH AZTEC GOLD BASE

ACTIVE INGREDIENT

Lactic Acid....................................................................................... 2.5%

INERT INGREDIENTS:...................................................................... 87.5%

SKIN CONDITIONING SYSTEM:

(contains glycerin)......................................................................... 10.0%

TOTAL:............................................................................................100.0%

208 L (55 US GAL)

Aztec GoldTM is a Trademark of Ecolab Inc.

St Paul, MN 55102 • Made in USA http://www.ecolab.com

Patent Pending

Foreign Patents Pending